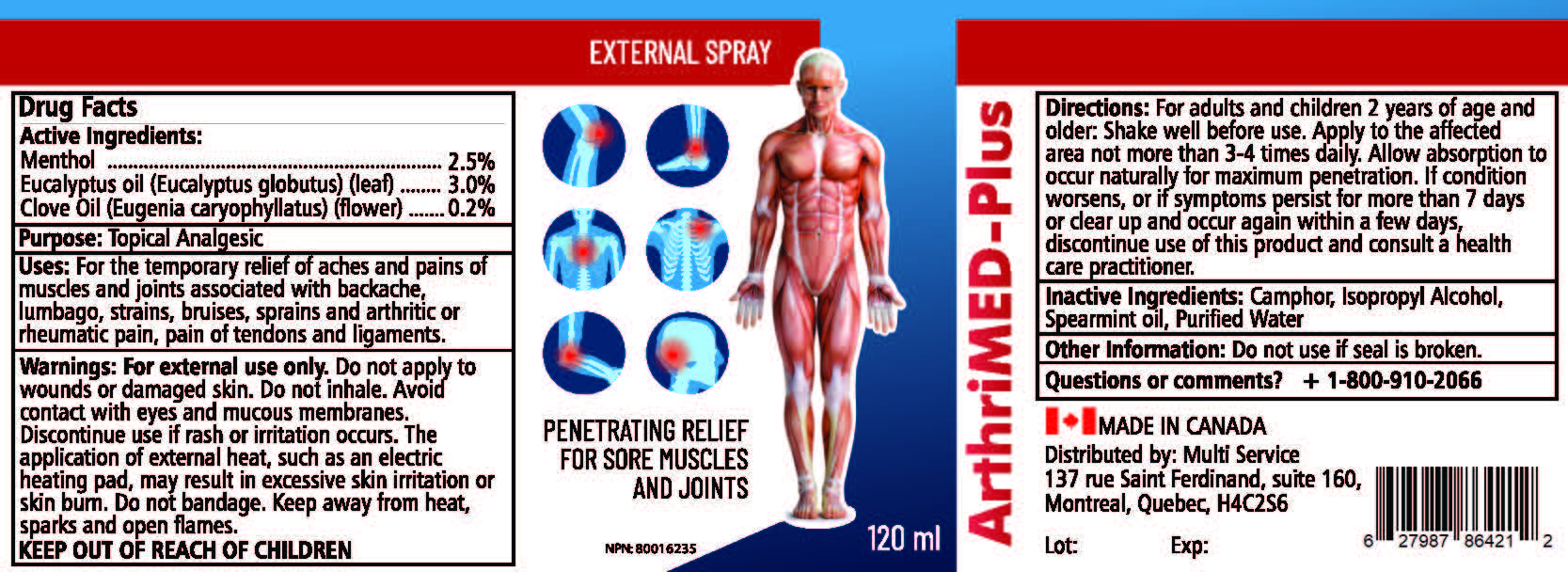 DRUG LABEL: ArthriMed-Plus
NDC: 82760-004 | Form: SPRAY
Manufacturer: Multi Service
Category: otc | Type: HUMAN OTC DRUG LABEL
Date: 20221117

ACTIVE INGREDIENTS: MENTHOL 2.5 g/100 g; EUCALYPTUS OIL 3 g/100 g; CLOVE OIL 0.2 g/100 g
INACTIVE INGREDIENTS: CAMPHOR (SYNTHETIC); ISOPROPYL ALCOHOL; PEPPERMINT OIL; WATER; WEST INDIAN LEMONGRASS OIL

ArthriMed-Plus Spray

Active Ingredients

Menthol 2.5%

Encalyptus oil (Eucalyptus globutus) (leaf) 3%

Clove Oil (Eugenia caryophyllatus) (leaf) 0.2%

Purpose

Topical Analgesic

Uses

For the temporary relief of aches and pains of muscles and joints associated with backache, lumbago,strains, bruises,sprains and arthritic or rheumatic pain, pain of tendons and ligaments.

Warnings

For external use only. Do not apply to wounds or damaged skin. Do not inhale. Avoid contact with eyes and mucous membranes. Discontinue use if rash or irritation occurs. The application of external heat, such as an electric heating pad, may result in excessive skin irritation or skin burn. Do not bandage. Keep away from heat, sparks and open flames.

Directions

For adults and children 2 years of age and older: Shake well before use. Apply to the affected area not more than 3-4 times daily. Allow absorption to occur naturally for maximum penetration. If condition worsens, or if symptoms persist for more than 7 days or clear up and occur again within a few days, discontinue use of this product and consult a health care practitioner.

Inactive Ingredients

Camphor, Lemongrass, Isopropyl Alcohol, Peppermint Oil, Purified Water

Other Information

Do not use if seal is broken.

Questions or comments?

info@multiservice.work

Principal Display Panel

Made in Canada

ArthriMed-Plus

Spray

Net Wt. 120 ml